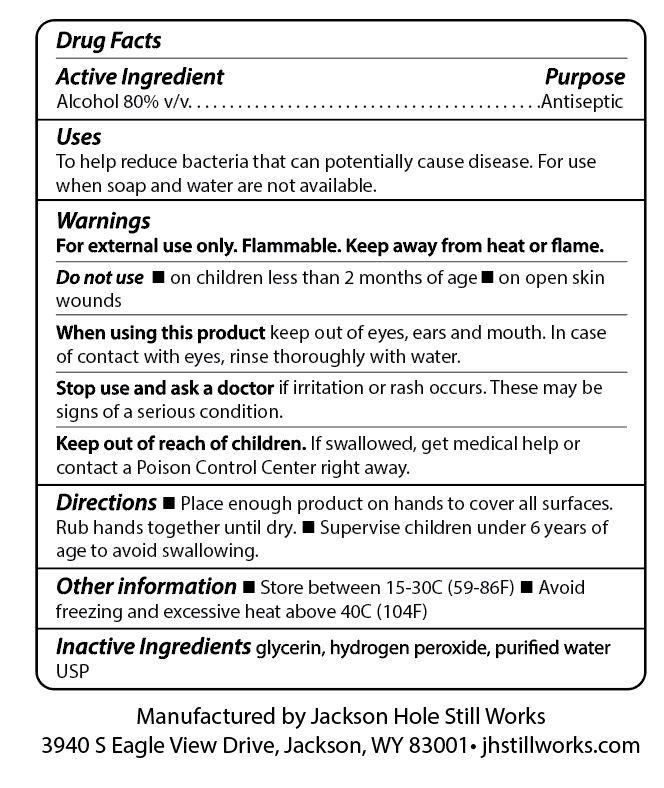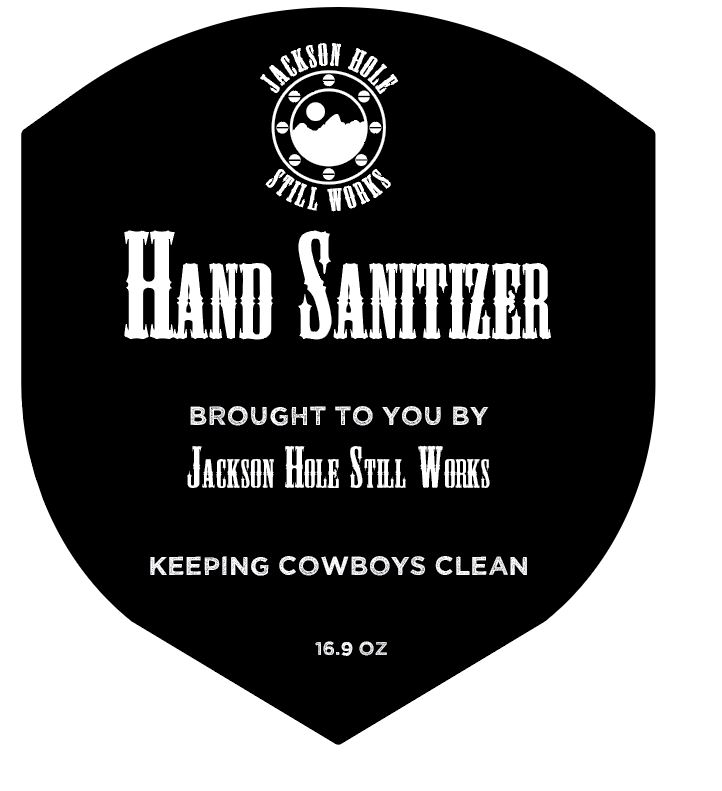 DRUG LABEL: Jackson Hole Still Works Hand Sanitizer
NDC: 74043-0001 | Form: LIQUID
Manufacturer: Jackson Hole Distillery, LLC
Category: otc | Type: HUMAN OTC DRUG LABEL
Date: 20200330

ACTIVE INGREDIENTS: ALCOHOL 8333 mL/10000 mL
INACTIVE INGREDIENTS: GLYCEROL FORMAL 145 mL/10000 mL; HYDROGEN PEROXIDE 417 mL/10000 mL; WATER 1105 mL/10000 mL

Active Ingredient and Back Label

Active Ingredient

Alcohol 80% v/v ... Antiseptic

Purpose section

Uses

To help reduce bacteria that can potentially cause disease. For use when soap and water are not available.

Warnings

For external use only. Flammable. Keep away from heat or flame.

Do not use

- on children less than 2 months of age
- on open skin wounds

When using this product

keep out of eyes, ears and mouth. In case of contact with eyes, rinse thoroughly with water.

Stop use and ask a dooctor

Stop use and ask a doctor

if irritation or rash occurs. These may be signs of a serious condition.

Keep out of reach of children

If swallowed, get medical help or contact a Poison Control Center right away.

Directions

- Place enough product on hands to cover all surfaces. Rub hands together until dry.
- Supervise children under 6 years of age to avoid swallowing.

Other information

- Store between 15-30C (59-86F)
- Avoid freezing and excessive heat above 40C (104F)

Inactive Ingredients

glycerin, hydrogen peroxide, purified water USP

Dosage and administration

Directions

- Place enough product on hands to cover all surfaces. Rub hands together until dry.
- Supervise children under 6 years of age to avoid swallowing.

Warnings Section

Warnings

For external use only. Flammable. Keep away from heat or flame.

Do not use

- on children less than 2 months of age
- on open skin wounds

When using this product keep out of eyes, ears and mouth. In case of contact with eyes, rinse thoroughly with water.

Stop use and ask a doctor if irritation or rash occurs. These may be signs of a serious condition.

Keep out of reach of children. If swallowed, get medical help or contact a Poison Control Center right away.

Indications & Usage

Uses

Hand sanitizer to help reduce bacteria that can potentially cause disease. For use when soap and water are not available.

Directions

- Place enough product on hands to cover all surfaces. Rub hands together until dry.
- Supervise children under 6 years of age to avoid swallowing.

Principal display panel & Front label

[Jackson Hole Still Works logo]

HAND SANITIZER

BROUGHT TO YOU BY

JACKSON HOLE STILL WORKS

KEEPING COWBOYS CLEAN

16.9 OZ